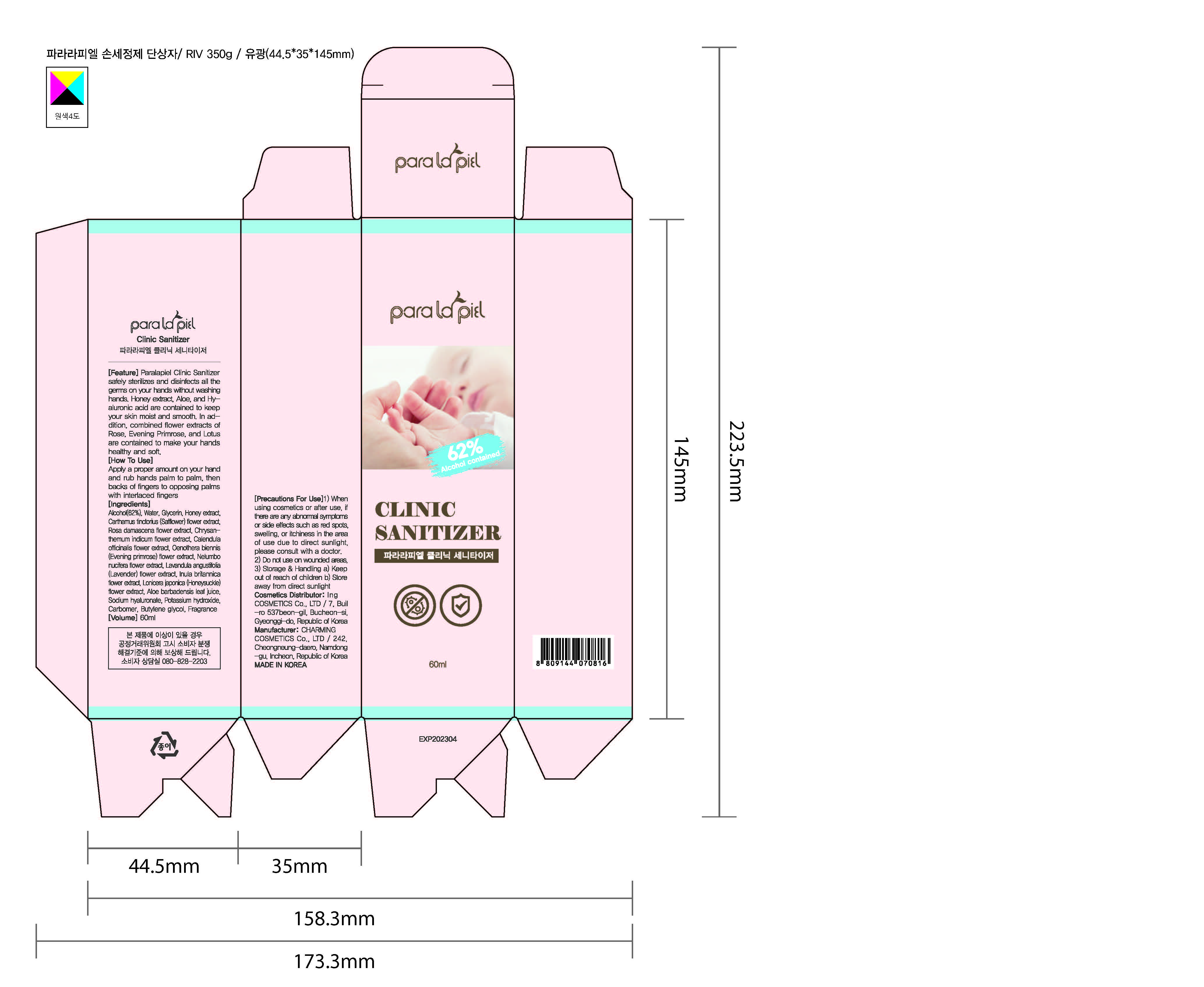 DRUG LABEL: Paralapiel Clinic Sanitizer
NDC: 77499-0001 | Form: GEL
Manufacturer: Charming Cosmetics. Co. Ltd
Category: otc | Type: HUMAN OTC DRUG LABEL
Date: 20200513

ACTIVE INGREDIENTS: ALCOHOL 37.2 mL/60 mL
INACTIVE INGREDIENTS: GLYCERIN; ALOE; CARBOMER HOMOPOLYMER, UNSPECIFIED TYPE; WATER; HYALURONIC ACID; BUTYLENE GLYCOL

Drug Facts

ACTIVE INGREDIENT

Alcohol

INACTIVE INGREDIENT

Water, Glycerin, Honey extract, Carthamus tinctorius (Safflower) flower extract, Rosa damascena flower extract, Chrysanthemum indicum flower extract, Calendula officinalis flower extract, Oenothera biennis (Evening primrose) flower extract, Nelumbo nucifera flower extract, Lavandula angustifolia (Lavender) flower extract, Inula britannica flower extract, Lonicera japonica (Honeysuckle) flower extract, Aloe barbadensis leaf juice, Sodium hyaluronate, Potassium hydroxide, Carbomer, Butylene glycol, Fragrance

PURPOSE

Antiseptic

KEEP OUT OF REACH OF THE CHILDREN

INDICATIONS AND USAGE

Handling : Use normal good handling procedures.

Storage : Keep containers tightly closed, away from heat and light and store at a cool and dry place.

WARNINGS

For external use only. Flammable, Keep away from fire or flames.
Do not use

■ in children less than 2 months of age

■ on open skin wounds
when using this product keep out of eyes, ears, and mouth.
Stop use and ask a doctor if irritation or rash occurs. these may be signs of a serious condition.
Keep out of reach of children. if swallowed, get medical help or contact a poison control center right away.

DOSAGE AND ADMINISTRATION

Apply a proper amount on your hand and rub hands palm to palm, then backs of fingers to opposing palms with interlaced fingers.